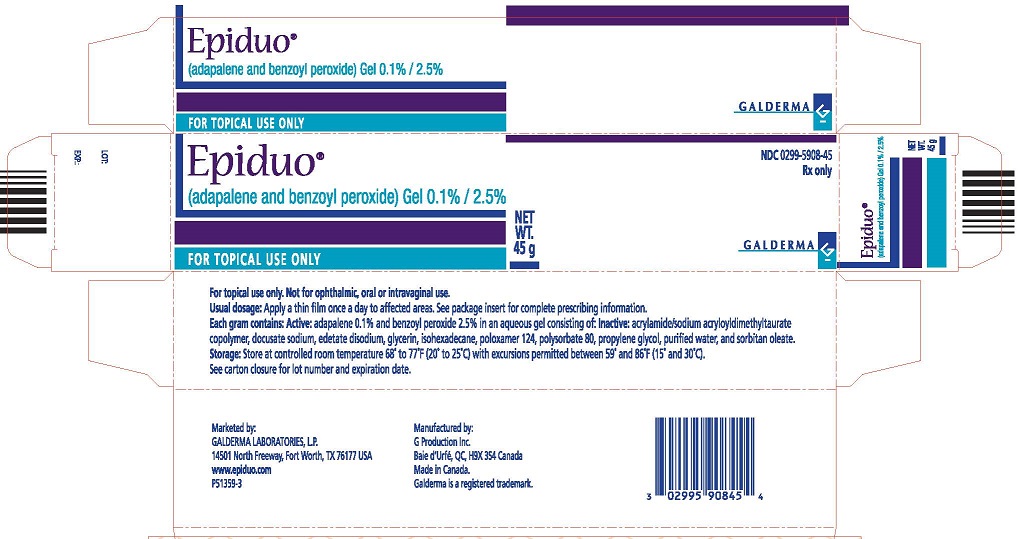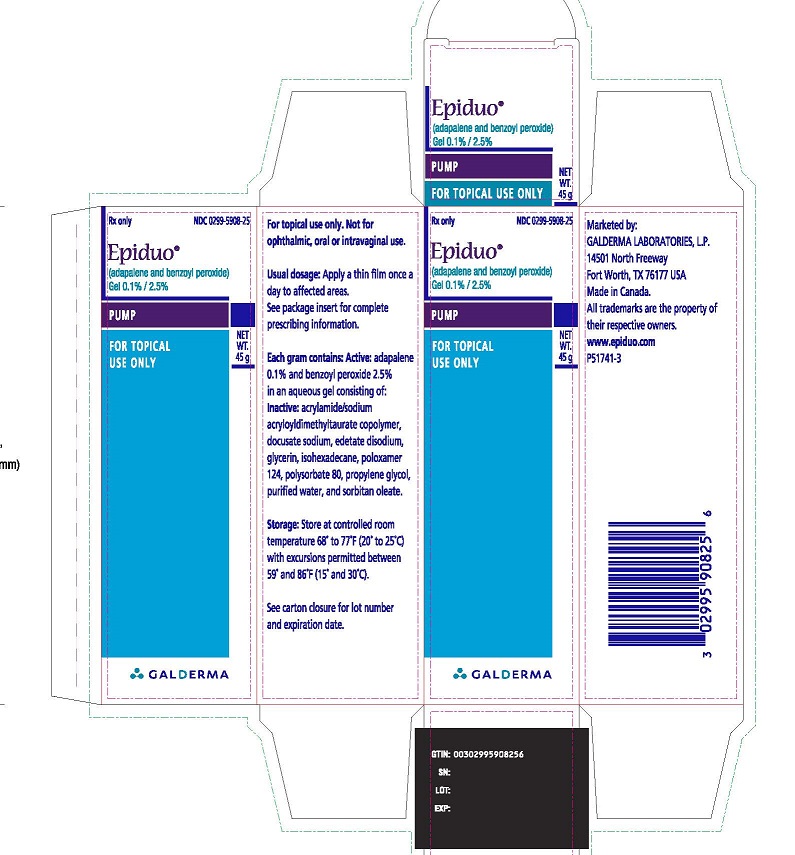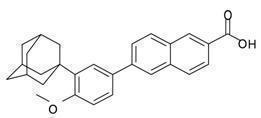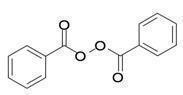 DRUG LABEL: EPIDUO
NDC: 0299-5908 | Form: GEL
Manufacturer: Galderma Laboratories, L.P.
Category: prescription | Type: HUMAN PRESCRIPTION DRUG LABEL
Date: 20241024

ACTIVE INGREDIENTS: ADAPALENE 1 mg/1 g; BENZOYL PEROXIDE 25 mg/1 g
INACTIVE INGREDIENTS: DOCUSATE SODIUM; EDETATE DISODIUM; GLYCERIN; ISOHEXADECANE; POLOXAMER 124; POLYSORBATE 80; PROPYLENE GLYCOL; WATER; SORBITAN MONOOLEATE

HIGHLIGHTS OF PRESCRIBING INFORMATION

These highlights do not include all the information needed to use EPIDUO Gel safely and effectively. See full prescribing information for EPIDUO Gel.
EPIDUO®(adapalene and benzoyl peroxide) Gel 0.1% / 2.5% For topical use
Initial U.S. Approval: 2008

1 INDICATIONS AND USAGE

EPIDUO gel is a combination of adapalene, a retinoid, and benzoyl peroxide, and is indicated for the topical treatment of acne vulgaris in patients 9 years of age and older. (1)

2 DOSAGE AND ADMINISTRATION

EPIDUO gel is not for oral, ophthalmic, or intravaginal use. (2)
Apply a thin film of EPIDUO gel to affected areas of the face and/or trunk once daily after washing. Use a pea-sized amount for each area of the face (e.g., forehead, chin, each cheek). Avoid the eyes, lips and mucous membranes. (2)

3 DOSAGE FORMS AND STRENGTHS

Each gram of EPIDUO gel contains 1 mg (0.1%) adapalene and 25 mg (2.5%) benzoyl peroxide. (3)

4 CONTRAINDICATIONS

None. (4)

5 WARNINGS AND PRECAUTIONS

Ultraviolet Light and Environmental Exposure: Avoid exposure to sunlight and sunlamps. Wear sunscreen when sun exposure cannot be avoided. (5.1)

Erythema, scaling, dryness, stinging/burning, irritant and allergic contact dermatitis may occur with use of EPIDUO gel and may necessitate discontinuation. (5.2)

6 ADVERSE REACTIONS

Most commonly reported adverse events (≥1%) in patients treated with EPIDUO gel were dry skin, contact dermatitis, application site burning, application site irritation and skin irritation. (6)

To report SUSPECTED ADVERSE REACTIONS, contact Galderma Laboratories, L.P. at 1-866-735-4137, or FDA at 1-800-FDA-1088 or www.fda.gov/medwatch

FULL PRESCRIBING INFORMATION

1 INDICATIONS AND USAGE

EPIDUO gel is indicated for the topical treatment of acne vulgaris in patients 9 years of age and older.

2 DOSAGE AND ADMINISTRATION

For topical use only; EPIDUO gel is not for oral, ophthalmic, or intravaginal use.

Apply a thin film of EPIDUO gel to affected areas of the face and/or trunk once daily after washing. Use a pea-sized amount for each area of the face (e.g., forehead, chin, each cheek). Avoid the eyes, lips and mucous membranes.

3 DOSAGE FORMS AND STRENGTHS

Each gram of EPIDUO gel contains 1 mg (0.1%) adapalene and 25 mg (2.5%) benzoyl peroxide in a white to very pale yellow, opaque, aqueous based gel.

4 CONTRAINDICATIONS

None

5 WARNINGS AND PRECAUTIONS

5.1 Ultraviolet Light and Environmental Exposure

Exposure to sunlight, including sunlamps, should be minimized during the use of EPIDUO gel. Patients with high levels of sun exposure and those with inherent sensitivity to sun should exercise particular caution. Use of sunscreen products and protective apparel, (e.g., hat) are recommended when exposure cannot be avoided. Weather extremes, such as wind or cold, may be irritating to patients under treatment with EPIDUO gel.

5.2 Local Cutaneous Reactions

Erythema, scaling, dryness, and stinging/burning may be experienced with use of EPIDUO gel. These are most likely to occur during the first four weeks of treatment, are mostly mild to moderate in intensity, and usually lessen with continued use of the medication. Irritant and allergic contact dermatitis may occur. Depending upon the severity of these adverse reactions, patients should be instructed to use a moisturizer, reduce the frequency of the application of EPIDUO gel, or discontinue use. The product should not be applied to cuts, abrasions, eczematous or sunburned skin. As with other retinoids, use of "waxing" as a depilatory method should be avoided on skin treated with EPIDUO gel.

Avoid concomitant use of other potentially irritating topical products (medicated or abrasive soaps and cleansers, soaps and cosmetics that have strong skin-drying effect and products with high concentrations of alcohol, astringents, spices, or limes).

6 ADVERSE REACTIONS

6.1 Clinical Studies Experience

Because clinical studies are conducted under widely varying conditions, adverse reaction rates observed in the clinical studies of a drug cannot be directly compared to rates in the clinical studies of another drug and may not reflect the rates observed in practice.

During clinical trials, 1401 subjects were exposed to EPIDUO gel. A total of 1036 subjects with acne vulgaris, 12 years and older, were treated once daily for 12 weeks to 12 months. Related adverse events reported within 12 weeks of treatment and in at least 1% of subjects treated with EPIDUO gel and those reported in subjects treated with the vehicle gel are presented in Table 1:

Table 1. Drug Related Adverse Events Reported in Clinical Trials by at Least 1% of Patients Treated For 12 Weeks
System Organ Class/Preferred Term | EPIDUO Gel N=564 | Vehicle Gel N=489
Subjects with AE(s) | 14% | 4%
Dry skin | 7% | 2%
Contact dermatitis | 3% | <1%
Application site burning | 2% | <1%
Application site irritation | 1% | <1%
Skin irritation | 1% | 0%

Local tolerability evaluations, presented in Table 2, were conducted at each study visit in clinical trials by assessment of erythema, scaling, dryness, burning, and stinging.

Table 2. Incidence of Local Cutaneous Irritation in Controlled Clinical Trials (N = 553) Treatment Emergent Signs and Symptoms
 | Maximum Severity During Treatment |  |  | End of Treatment Severity (12 weeks)
 | Mild | Moderate | Severe | Mild | Moderate | Severe
Erythema | 27% | 13% | 1% | 8% | 2% | 1%
Scaling | 35% | 11% | 1% | 9% | 1% | <1%
Dryness | 41% | 13% | 1% | 10% | 2% | <1%
Stinging/burning | 41% | 15% | 3% | 7% | 2% | 1%

Analysis over the 12-week period showed that local tolerability scores for erythema, scaling, dryness, and stinging/burning peaked at Week 1 of therapy and decreased thereafter.

During a pediatric clinical trial, 285 children with acne vulgaris, 9 to 11 years of age were treated with EPIDUO gel or with the vehicle gel once daily for 12 weeks. Overall, the safety profile of EPIDUO gel in these subjects is comparable to the safety profile observed in older subjects 12 years of age and above, both in the nature and frequency of the observed adverse events.

Analysis of local tolerability evaluations shows similar incidence of treatment emergent signs and symptoms as in subjects 12 years of age and above, with local tolerability signs and symptoms peaking during the first week and decreasing over time.

6.2 Postmarketing Experience

The following adverse reactions have been identified during postapproval use of EPIDUO gel: eyelid edema, sunburn, blister, pain of skin, pruritus, swelling face, conjunctivitis, skin discoloration, rash, eczema, throat tightness and allergic contact dermatitis. Because these reactions are reported voluntarily from a population of uncertain size, it is not always possible to reliably estimate their frequency or establish a causal relationship to drug exposure.

7 DRUG INTERACTIONS

Concomitant topical acne therapy should be used with caution because a possible cumulative irritancy effect may occur, especially with the use of peeling, desquamating, or abrasive agents.

No formal drug-drug interaction studies were conducted with EPIDUO gel.

8 USE IN SPECIFIC POPULATIONS

8.1 Pregnancy

Pregnancy Category C. There are no well-controlled trials in pregnant women treated with EPIDUO gel. Animal reproduction studies have not been conducted with the combination gel or benzoyl peroxide. Furthermore, such studies are not always predictive of human response; therefore, EPIDUO gel should be used during pregnancy only if the potential benefit justifies the risk to the fetus.

No teratogenic effects were observed in rats treated with oral doses of 0.15 to 5.0 mg adapalene/kg/day, up to 25 times (mg/m^2/day) the maximum recommended human dose (MRHD) of 2 grams of EPIDUO gel. However, teratogenic changes were observed in rats and rabbits when treated with oral doses of ≥ 25 mg adapalene/kg/day representing 123 and 246 times MRHD, respectively. Findings included cleft palate, microphthalmia, encephalocele and skeletal abnormalities in rats; and umbilical hernia, exophthalmos and kidney and skeletal abnormalities in rabbits.

Dermal teratology studies conducted in rats and rabbits at doses of 0.6-6.0 mg adapalene/kg/day [25-59 times (mg/m^2) the MRHD] exhibited no fetotoxicity and only minimal increases in supernumerary ribs in both species and delayed ossification in rabbits.

8.3 Nursing Mothers

It is not known whether adapalene or benzoyl peroxide is excreted in human milk following use of EPIDUO gel. Because many drugs are excreted in human milk, caution should be exercised when EPIDUO gel is administered to a nursing woman.

8.4 Pediatric Use

Safety and effectiveness of EPIDUO gel in pediatric patients under the age of 9 have not been established.

8.5 Geriatric Use

Clinical studies of EPIDUO gel did not include sufficient numbers of subjects aged 65 and over to determine whether they respond differently from younger subjects.

11 DESCRIPTION

EPIDUO (adapalene and benzoyl peroxide) gel, 0.1%/2.5% is a white to very pale yellow, opaque gel for topical use containing adapalene 0.1% and benzoyl peroxide 2.5%.

Active: Adapalene, a synthetic retinoid, is a naphthoic acid derivative with retinoid-like properties. The chemical name for adapalene is (6-[3-(1-adamantyl)-4-methoxyphenyl]-2- naphthoic acid). It has the following structural formula:

Adapalene:

Molecular formula: C28H28O3Molecular weight: 412.5

Benzoyl Peroxide is a highly lipophilic oxidizing agent that localizes in both bacterial and keratinocyte cell membranes. The chemical name for benzoyl peroxide is dibenzoyl peroxide. It has the following structural formula:

Benzoyl Peroxide:

Molecular formula: C14H10O4Molecular weight: 242.23

EPIDUO gel contains the following inactive ingredients: acrylamide/sodium acryloyldimethyltaurate copolymer, docusate sodium, edetate disodium, glycerin, isohexadecane, poloxamer 124, polysorbate 80, propylene glycol, purified water, and sorbitan oleate.

12 CLINICAL PHARMACOLOGY

12.1 Mechanism of Action

Adapalene

Adapalene binds to specific retinoic acid nuclear receptors but does not bind to cytosolic receptor protein. Biochemical and pharmacological profile studies have demonstrated that adapalene is a modulator of cellular differentiation, keratinization and inflammatory processes. However, the significance of these findings with regard to the mechanism of action of adapalene for the treatment of acne is unknown.

Benzoyl peroxide

Benzoyl peroxide is an oxidizing agent with bactericidal and keratolytic effects.

12.2 Pharmacodynamics

Pharmacodynamics of EPIDUO gel is unknown.

12.3 Pharmacokinetics

A pharmacokinetic study was conducted in 10 adult subjects with acne vulgaris who were treated once daily for 30 days with 2 grams/day of EPIDUO gel applied to 1000 cm^2of acne involved skin, (face, chest, and upper back).

Two subjects (20%) had quantifiable adapalene plasma concentrations above the limit of quantification (LOQ = 0.1ng/mL). The highest adapalene Cmaxand AUC0-24hwas 0.21 ng/mL and 1.99 ng•h/mL, respectively. Excretion of adapalene appears to be primarily by the biliary route. Pharmacokinetics of EPIDUO gel in pediatric subjects have not been evaluated.

Benzoyl peroxide is absorbed by the skin where it is converted to benzoic acid and eliminated in the urine.

13 NONCLINICAL TOXICOLOGY

13.1 Carcinogenesis, Mutagenesis, Impairment of Fertility

No carcinogenicity, photocarcinogenicity, genotoxicity, or fertility studies were conducted with EPIDUO gel.

Carcinogenicity studies with adapalene have been conducted in mice at topical doses of 0.4, 1.3, and 4.0 mg/kg/day (1.2, 3.9, and 12 mg/m^2/day), and in rats at oral doses of 0.15, 0.5, and 1.5 mg/kg/day (0.9, 3.0, and 9.0 mg/m^2/day). In terms of body surface area, the highest dose levels are 9.8 (mice) and 7.4 times (rats) the MRHD of 2 grams of EPIDUO gel. In the rat study, an increased incidence of benign and malignant pheochromocytomas in the adrenal medulla of male rats was observed.

No significant increase in tumor formation was observed in rodents topically treated with 15-25% benzoyl peroxide carbopol gel (6-10 times the concentration of benzoyl peroxide in EPIDUO gel) for two years. Rats received maximum daily applications of 138 (males) and 205 (females) mg benzoyl peroxide/kg. In terms of body surface area, these levels are 27-40 times the MRHD. Similar results were obtained in mice topically treated with 25% benzoyl peroxide carbopol gel for 56 weeks followed by intermittent treatment with 15% benzoyl peroxide carbopol gel for the rest of the 2 year study period, and in mice topically treated with 5% benzoyl peroxide carbopol gel for two years.

The role of benzoyl peroxide as a tumor promoter has been well established in several animal species. However, the significance of this finding in humans is unknown.

In a photocarcinogenicity study conducted with 5% benzoyl peroxide carbopol gel, no increase in UV-induced tumor formation was observed in hairless mice topically treated for 40 weeks.

No photocarcinogenicity studies were conducted with adapalene. However, animal studies have shown an increased tumorigenic risk with the use of pharmacologically similar drugs (e.g., retinoids) when exposed to UV irradiation in the laboratory or sunlight. Although the significance of these findings to humans is not clear, patients should be advised to avoid or minimize exposure to either sunlight or artificial irradiation sources.

Adapalene did not exhibit mutagenic or genotoxic effects in vitro(Ames test, Chinese hamster ovary cell assay, mouse lymphoma TK assay) or in vivo(mouse micronucleus test).

Bacterial mutagenicity assays (Ames test) with benzoyl peroxide has provided mixed results, mutagenic potential was observed in a few but not in a majority of investigations. Benzoyl peroxide has been shown to produce single-strand DNA breaks in human bronchial epithelial and mouse epidermal cells, it has caused DNA-protein cross-links in the human cells, and has also induced a dose-dependent increase in sister chromatid exchanges in Chinese hamster ovary cells.

In rat oral studies, 20 mg adapalene/kg/day (120 mg/m^2/day; 98 times the MRHD based on mg/m^2/day comparison) did not affect the reproductive performance and fertility of F0males and females, or growth, development and reproductive function of F1offspring.

No fertility studies were conducted with benzoyl peroxide.

14 CLINICAL STUDIES

The safety and efficacy of EPIDUO gel applied once daily for the treatment of acne vulgaris were assessed in two 12-week, multicenter, controlled clinical studies of similar design, comparing EPIDUO gel to the gel vehicle in acne subjects.Treatment response was defined as the percent of subjects who had a two grade improvement and rated ‘Clear’ and ‘Almost Clear’ at Week 12 based on the Investigator's Global Assessment (IGA) and mean absolute change from baseline at Week 12 in both inflammatory and non-inflammatory lesion counts. An IGA score of 'Clear' corresponded to residual hyperpigmentation and erythema may be present. An IGA score of ‘Almost Clear’ corresponded to a few scattered comedones and a few small papules.In Study 1, 517 subjects were randomized to EPIDUO gel, adapalene 0.1% in vehicle gel, benzoyl peroxide 2.5% in vehicle gel, or vehicle gel. The median age of these 517 subjects was 15 years old and 60% were males. At baseline subjects had between 20 to 50 inflammatory lesions and 30 to 100 non-inflammatory lesions. The majority of subjects had a baseline IGA score of ‘Moderate’ which corresponded to more than half of the face is involved, many comedones, papules and pustules. The efficacy results at week 12 are presented in Table 3.In Study 2, 1668 subjects were randomized to EPIDUO gel, adapalene 0.1% in vehicle gel, benzoyl peroxide 2.5% in vehicle gel, or vehicle gel. The median age of subjects was 16 years old and 49% were males. At baseline subjects had between 20 to 50 inflammatory lesions and 30 to 100 non-inflammatory lesions as well as an Investigator Global Assessment score of ‘Moderate’. The efficacy results at week 12 are presented in Table 3.In Study 3, 285 pediatric subjects 9 to 11 years of age were randomized to EPIDUO gel or vehicle gel. The median age of subjects was 11 years and 24% were males. At baseline, subjects had a minimum of 20 but not more than 100 total lesions (inflammatory and/or non-inflammatory) with an Investigator Global Assessment score of 'Moderate'. The efficacy results at week 12 are presented in Table 3.

Table 3: Clinical Efficacy of EPIDUO Gel at Week 12
Study 1
 | EPIDUO gel (N=149) | Adapalene 0.1% in Vehicle gel (N=148) | Benzoyl Peroxide 2.5% in Vehicle gel (N=149) | Vehicle gel (N=71)
IGA: Two Grade Improvement and Clear Almost Clear | 32 (21.5%) | 18 (12.2%) | 18 (12.1%) | 4 (5.6%)
Inflammatory Lesions: Mean Absolute (Percent) Change | 16.0 (52.4%) | 11.4 (39.9%) | 10.5 (35.8%) | 9.5 (31.8%)
Non-inflammatory Lesions: Mean Absolute (Percent) Change | 23.4 (45.9%) | 15.2 (29.6%) | 13.7 (32.2%) | 13.2 (27.8%)

Study 2
 | EPIDUO gel (N=415) | Adapalene 0.1% in Vehicle gel (N=420) | Benzoyl Peroxide 2.5% in Vehicle gel (N=415) | Vehicle gel (N=418)
IGA: Two Grade Improvement and Clear or Almost Clear | 125 (30.1%) | 83 (19.8%) | 92 (22.2%) | 47 (11.3%)
Inflammatory Lesions: Mean Absolute (Percent) Change | 15.4 (53.4%) | 12.3 (41.7%) | 13.7 (47.6%) | 8.7 (30.2%)
Non-inflammatory Lesions: Mean Absolute (Percent) Change | 24.6 (48.1%) | 21.0 (40.8%) | 19.2 (37.2%) | 11.3 (23.2%)

In both Studies 1 and 2 the treatment effect was smaller in subjects with a small number of baseline lesions than in subjects with a large number of baseline lesions.

Study 3
 | EPIDUO Gel N=142 | Vehicle Gel N=143
IGA: Two Grade Improvement and Clear or Almost Clear | 67 (47.2%) | 22 (15.4%)
Inflammatory Lesions: Mean Absolute (Percent) Change | 7.4 (36.0%) | 0.7 (-13.2%)*
Non-inflammatory Lesions: Mean Absolute (Percent) Change | 20.2 (54.7%) | 2.9 (2.3%)

* -That is, a mean percent increase of 13.2%

16 HOW SUPPLIED/STORAGE AND HANDLING

EPIDUO (adapalene and benzoyl peroxide) gel 0.1% / 2.5% is white to very pale yellow in color and opaque in appearance, and is supplied as follows:

45 gram tube NDC 0299-5908-45
45 gram pump NDC 0299-5908-25

Storage and handling

- Store at 25ºC; excursions permitted to 15º - 30ºC (59º - 86ºF).

- Protect from light.

- Keep out of reach of children.

- Keep away from heat.

- Keep tube tightly closed.

17 PATIENT COUNSELING INFORMATION

[See FDA approved Patient Labeling (Patient Information)]

Information for Patients

- Advise patients to cleanse the area to be treated with a mild or soapless cleanser; pat dry. Apply EPIDUO gel as a thin layer, avoiding the eyes, lips and mucous membranes.

- Advise patients not to use more than the recommended amount and not to apply more than once daily as this will not produce faster results, but may increase irritation.

- EPIDUO gel may cause irritation such as erythema, scaling, dryness, stinging or burning.

- Advise patients to minimize exposure to sunlight, including sunlamps.

- Recommend the use of sunscreen products and protective apparel, (e.g., hat) when exposure cannot be avoided.

- EPIDUO gel may bleach hair and colored fabric.

Patient Information
EPIDUO®(Ep-E-Do-Oh)
(adapalene and benzoyl peroxide)
gel 0.1%/2.5%

Important:For use on the skin only (topical). Do not use EPIDUO gel in or on your mouth, eyes, or vagina.

Read this Patient Information leaflet about EPIDUO gel before you start using it and each time you get a refill. There may be new information. This leaflet does not take the place of talking with your doctor about your treatment or your medical condition. If you have any questions about EPIDUO gel, talk with your doctor or pharmacist.

What is EPIDUO gel?
EPIDUO gel is a prescription medicine for skin use only (topical) used to treat acne vulgaris in people 9 years of age and older.

Acne vulgaris is a condition in which the skin has blackheads, whiteheads and pimples.

It is not known if EPIDUO gel is safe and effective in children younger than 9 years old.

What should I tell my doctor before using EPIDUO gel?
Before you use EPIDUO gel, tell your doctor if you:

- have other skin problems, including cuts or sunburn
- have any other medical conditions
- are pregnant or planning to become pregnant. It is not known if EPIDUO gel can harm your unborn baby. Talk to your doctor if you are pregnant or plan to become pregnant.
- are breastfeeding or plan to breastfeed. It is not known if EPIDUO gel passes into your breast milk and if it can harm your baby. Talk to your doctor about the best way to feed your baby if you use EPIDUO gel.

Tell your doctor about all the medicines you take,including prescription and nonprescription medicines, vitamins and herbal supplements.

Especially tell your doctor if you use any other medicine for acne. Using EPIDUO gel with topical medicines that contain sulfur, resorcinol or salicylic acid may cause skin irritation.

Know the medicines you take. Keep a list of them to show your doctor and pharmacist when you get a new medicine.

How should I use EPIDUO gel?

- Use EPIDUO gel exactly as your doctor tells you to use it. EPIDUO gel is for skin use only. Do not use EPIDUO gel in or on your mouth, eyes, or vagina.
- Apply EPIDUO gel 1 time a day.
- Do not use more EPIDUO gel than you need to cover the treatment area. Using too much EPIDUO gel or using it more than 1 time a day may increase your chance of skin irritation.

Applying EPIDUO gel:

- Wash the area where the gel will be applied with a mild cleanser and pat dry.
- EPIDUO gel comes in a tube and a pump. If you have been prescribed the:
  - Tube: Squeeze a small amount (about the size of a pea) of EPIDUO gel onto your fingertips and spread a thin layer over the affected area.
  - Pump: Depress the pump to dispense a small amount (about the size of a pea) of EPIDUO gel and spread a thin layer over the affected area.

What should I avoid while using EPIDUO gel?

- You should avoid spending time in sunlight or artificial sunlight, such as tanning beds or sunlamps. EPIDUO gel can make your skin sensitive to sun and the light from tanning beds and sunlamps. You should wear sunscreen and wear a hat and clothes that cover the areas treated with EPIDUO gel if you have to be in sunlight.
- You should avoid weather extremes such as wind and cold as this may cause irritation to your skin.
- You should avoid applying EPIDUO gel to cuts, abrasions and sunburned skin.
- You should avoid skin products that may dry or irritate your skin such as harsh soaps, astringents, cosmetics that have strong skin- drying effects and products containing high levels of alcohol.
- You should avoid the use of “waxing” as a hair removal method on skin treated with EPIDUO gel.
- EPIDUO gel may bleach your clothes or hair. Allow EPIDUO gel to dry completely before dressing to prevent bleaching of your clothes.

What are the possible side effects of EPIDUO gel?

EPIDUO gel may cause serious side effects including:

- Local skin reactions. Local skin reactions are most likely to happen during the first 4 weeks of treatment and usually lessen with continued use of EPIDUO gel. Signs and symptoms of local skin reaction include:
  - Redness
  - Dryness
  - Swelling
  - Scaling
  - Stinging or burning

Tell your doctor right away if these side effects continue for longer than 4 weeks or get worse, you may have to stop using EPIDUO gel.

Tell your doctor if you have any side effect that bothers you or that does not go away.

These are not all the possible side effects of EPIDUO gel. For more information, ask your doctor or pharmacist.

Call your doctor for medical advice about side effects. You may report side effects to FDA at 1-800-FDA-1088.

You may also report side effects to GALDERMA LABORATORIES, L.P. at 1-866-735-4137

How should I store EPIDUO gel?

- Store EPIDUO gel at room temperature, 68° - 77° F (20° - 25° C).
- Keep EPIDUO gel inside container and out of light and away from heat.

Keep EPIDUO gel and all medicines out of the reach of children.

General information about EPIDUO gel

Medicines are sometimes prescribed for purposes other than those listed in a Patient Information Leaflet. Do not use EPIDUO gel for a condition for which it was not prescribed. Do not give EPIDUO gel to other people, even if they have the same symptoms you have. It may harm them.

This Patient Information leaflet summarizes the most important information about EPIDUO gel. If you would like more information, talk with your doctor. You can also ask your doctor or pharmacist for information about EPIDUO gel that is written for health professionals.

What are the ingredients in EPIDUO gel?
Active ingredient: adapalene and benzoyl peroxide
Inactive ingredients: acrylamide/sodium acryloydimethyltaurate copolymer, docusate sodium, edetate disodium, glycerin, isohexadecane, poloxamer 124, polysorbate 80, propylene glycol, purified water and sorbitan oleate

Revised: January 2013

Marketed by:
GALDERMA LABORATORIES, L.P., Fort Worth, Texas 76177 USA
Manufactured by:
G Production Inc., Baie d’Urfé, QC, H9X 3S4 Canada
Made in Canada.
GALDERMA is a registered trademark.
P51740-2

PACKAGE LABEL 45 g PUMP

Rx Only
NDC 0299-5908-25
Epiduo®
(adapalene and benzoyl peroxide) Gel 0.1% / 2.5%
PUMP
FOR TOPICAL USE ONLY
NET WT. 45g
GALDERMA

For topical use only. Not for ophthalmic, oral or intravaginal use.
Usual dosage: Apply a thin film once a day to affected areas.
See package insert for complete prescribing information.
Each gram contains: Active:adapalene 0.1% and benzoyl peroxide 2.5% in an aqueous gel consisting of: Inactive:acrylamide/sodium acryloyldimethyltaurate copolymer, docusate sodium, edetate disodium, glycerin, isohexadecane, poloxamer 124, polysorbate 80, propylene glycol, purified water, and sorbitan oleate.
Storage:Store at controlled room temperature 68° to 77°F (20° to 25°C) with excursions permitted between 59° and 86°F (15° and 30°C).
See carton closure for lot number and expiration date.

Marketed by:
GALDERMA LABORATORIES, L.P.
14501 North Freeway, Fort Worth, TX 76177 USA
Made in Canada.
All trademarks are the property of their respective owners.
www.epiduo.com
P51741-3

PACKAGE LABEL

Epiduo®
(adapalene and benzoyl peroxide)
Gel 0.1% / 2.5%
FOR TOPICAL USE ONLY
NET WT. 45 g
NDC 0299-5908-45
Rx only
GALDERMA

For topical use only. Not for ophthalmic, oral or intravaginal use.

Usual dosage:Apply a thin film once a day to affected areas. See package insert for complete prescribing information.

Each gram contains Active:adapalene 0.1% and benzoyl peroxide 2.5% in an aqueous gel consisting of Inactive:acrylamide/sodium acryloyldimethyltaurate copolymer, docusate sodium, edetate disodium, glycerin, isohexadecane, poloxamer 124, polysorbate 80, propylene glycol, purified water, and sorbitan oleate.

Storage:Store at controlled room temperature 68° to 77°F (20° to 25°C) with excursions permitted between 59° and 86°F (15° and 30°C).
See carton closure for lot number and expiration date.

Marketed by:
GALDERMA LABORATORIES, L.P.
14501 North Freeway, Fort Worth, TX 76177 USA
www.epiduo.com
P51359-3
Manufactured by:
G Production Inc.
Baie d’Urfé, QC, H9X 3S4 Canada
Made in Canada.
Galderma is a registered trademark.